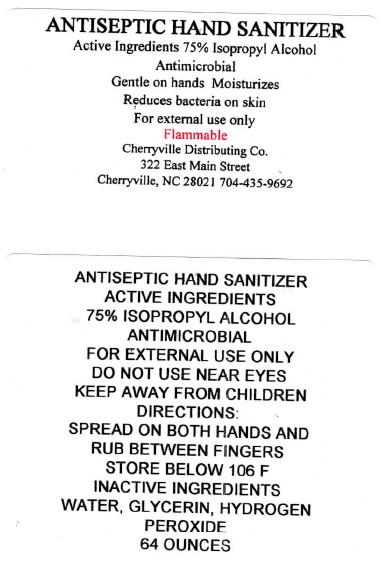 DRUG LABEL: ANTISEPTIC HAND SANITIZER
NDC: 90006-024 | Form: LIQUID
Manufacturer: Cherryville Distributing Company, Inc.
Category: otc | Type: HUMAN OTC DRUG LABEL
Date: 20200821

ACTIVE INGREDIENTS: ISOPROPYL ALCOHOL 75 mL/100 mL
INACTIVE INGREDIENTS: WATER; GLYCERIN; HYDROGEN PEROXIDE

ANTISEPTIC HAND SANITIZER

ACTIVE INGREDIENTS

75% ISOPROPYL ALCOHOL

PURPOSE

ANTIMICROBIAL

USES

Reduces Bacteria on skin

WARNINGS

FOR EXTERNAL USE ONLY

DO NOT USE NEAR EYES

Flammable

KEEP AWAY FROM CHILDREN

DIRECTIONS

SPREAD ON BOTH HANDS AND RUB BETWEEN FINGERS

INACTIVE INGREDIENTS

WATER, GLYCERIN, HYDROGEN PEROXIDE

STORAGE AND HANDLING

STORE BELOW 106 F

Gentle on hands Moisturizes

Cherryville Distributing Co.

322 East Main Street

Cherryville, NC 28021 704-435-9692